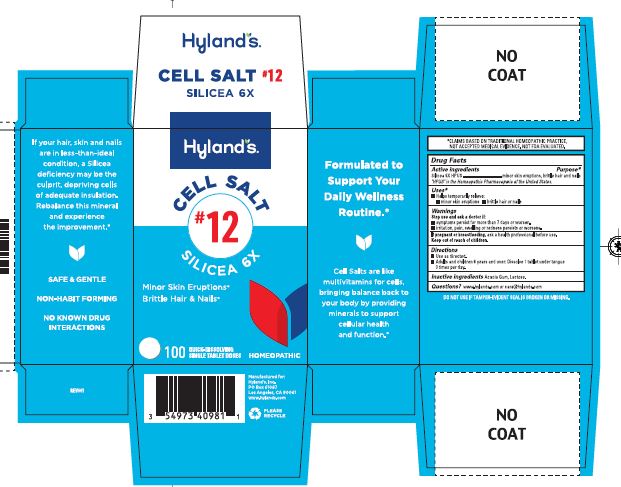 DRUG LABEL: Silicea 6X
NDC: 54973-4098 | Form: TABLET, SOLUBLE
Manufacturer: Hyland's Inc.
Category: homeopathic | Type: HUMAN OTC DRUG LABEL
Date: 20250227

ACTIVE INGREDIENTS: SILICON DIOXIDE 6 [hp_X]/1 1
INACTIVE INGREDIENTS: ACACIA; LACTOSE MONOHYDRATE

Cell Salt #12 Silicea 6X

PURPOSE

Minor Skin Eruptions, Brittle Hair or Nails

Drug Facts

Active ingredients | Purpose
Silicea 6X HPUS | minor skin eruptions, brittle hair and nails

"HPUS" is the Homeopathic Pharmacopoeia of the United States.

Uses

■ Temporarily relieves:
■ minor skin eruptions ■ brittle hair or nails

Warnings

Stop use and ask a doctor if

■ symptoms persist for more than 7 days or worsen.
■ irritation, pain, swelling or redness persists or worsens.

If pregnant or breastfeeding

Ask a health professional before use.

Directions

■ Use as directed.
■ Adults and children 6 years and over: Dissolve 1 tablet under tongue 3 times per day.

Inactive ingredients

Acacia Gum, Lactose.

Questions?

www.hylands.com or care@hylands.com

Package Label - 100 Tablets Bottle Carton

Hyland's

NATURALS™

CELL SALT

#12

SILICEA 6X

Minor Skin Eruptions*

Brittle Hair & Nails*

100

QUICK-DISSOLVING

SINGLE TABLET DOSES

HOMEOPATHIC